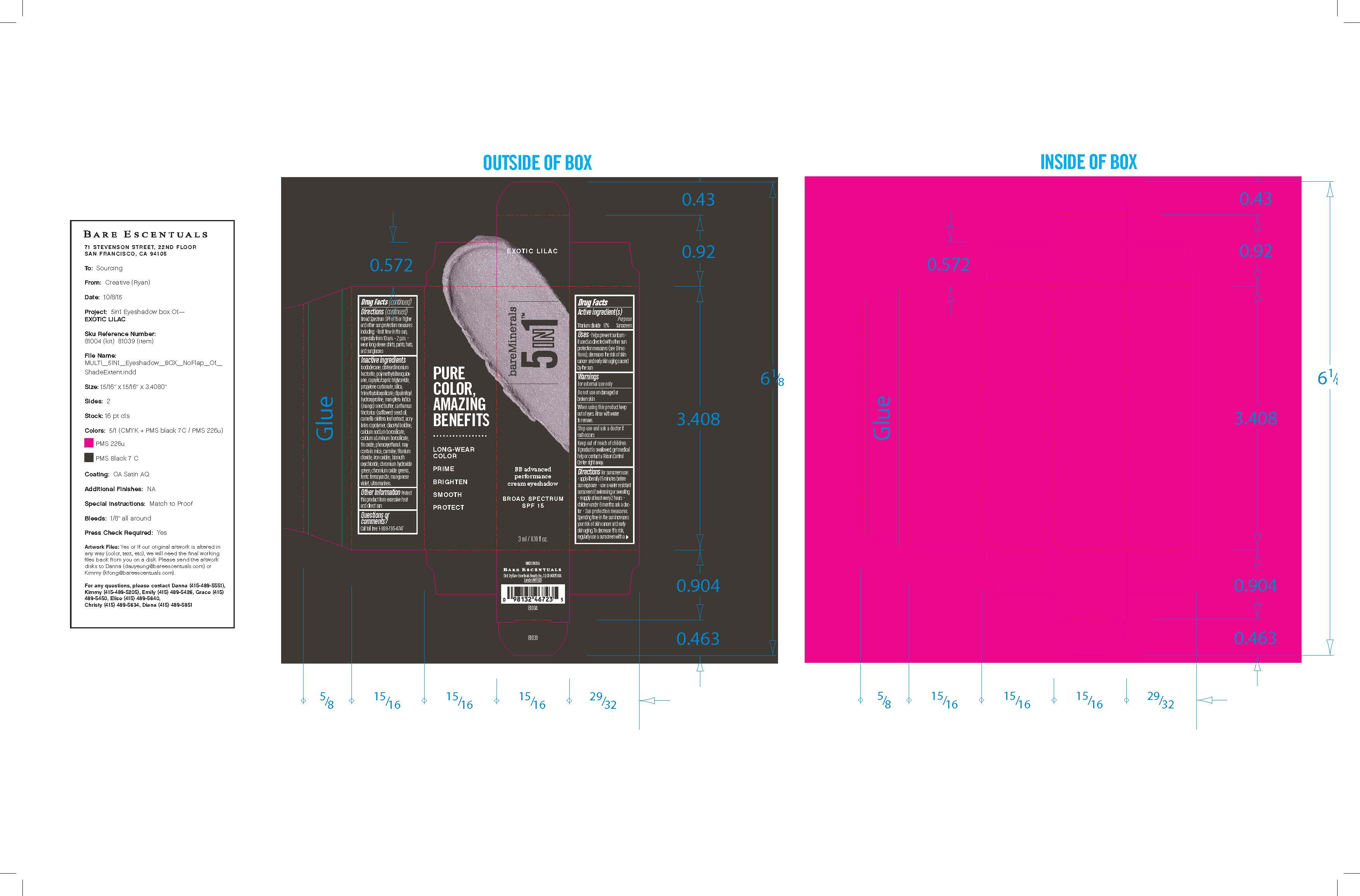 DRUG LABEL: Cream
NDC: 61354-080 | Form: CREAM
Manufacturer: Oxygen Development LLC
Category: otc | Type: HUMAN OTC DRUG LABEL
Date: 20230210

ACTIVE INGREDIENTS: TITANIUM DIOXIDE 17 mg/100 mg
INACTIVE INGREDIENTS: TRIMETHYLSILOXYSILICATE (M/Q 0.66); MANGO SEED OIL; ACRYLATES CROSSPOLYMER-6; ISODODECANE; MICA; DISTEARDIMONIUM HECTORITE; POLYMETHYLSILSESQUIOXANE (11 MICRONS); CAPRYLIC/CAPRIC/LAURIC TRIGLYCERIDE; PROPYLENE CARBONATE; SILICON DIOXIDE; DIPALMITOYL HYDROXYPROLINE

Bare Minerals 5 in 1 BB advanced performance cream eyeshadow broad spectrum spf 15 - Exotic Lilac

Active Ingredient

Titanium Dioxide 17%. Purpose: Sunscreen

Purpose

Sunscreen

Uses

helps prevent sunburn if used as directed with other sun protection measures. Decreased the risk of skin cancer and early skin aging caused by the sun

Warnings

for external use only

Do not use

on damaged or broken skin

When using

this product, keep out of eyes. Rinse with water to remove

Stop use

and ask a doctor if rash occurs

Keep out of reach of children

If product is swallowed, get medical help or contact a poison control center right away

Directions

for sunscreen use:

- apply liberally 15 minutes before sun exposure
- use a water resistant sunscreen if swimming or sweating
- reapply at least every 2 hours
- children under 6 months ask a doctor

Sun protection measures

spending time in the sun increases your risk of skin cancer and early skin aging. To decrease the risk regularly use a sunscreen with a broad spectrum SPF of 15 or higher and other sun protection measures including:

- limit time in the sun, especially from 10am - 2pm
- wear long-slevve shirts, pants, hats, and sunglasses

Inactive ingredients

isododecane, disteardimonium hectorite, Polymethylsilsesquioxane, Caprylic/Capric Triglyceride, propylene carbonate, silica, Trimethylsiloxysilicate, Dipalmitoyl Hydroxyproline, Mangifera Indica (Mango) Seed Butter, Carthamus Tinctorius (Safflower) Seed Oil, Camellia Oleifera Leaf Extract, Acrylates Copolymer, Diacetyl Boldine, Calcium Sodium Borosilicate, Calcium Aluminum Borosilicate, tin oxide, phenoxyethanol, may contain: mica, carmine, titanium dioxide, iron oxides, Bismuth Oxychloride,chromium hydroxide green, chromium oxide greens, ferric fenocyanide, manganese violet, ultramarines

other information

protect this product from excessive heat and direct sun